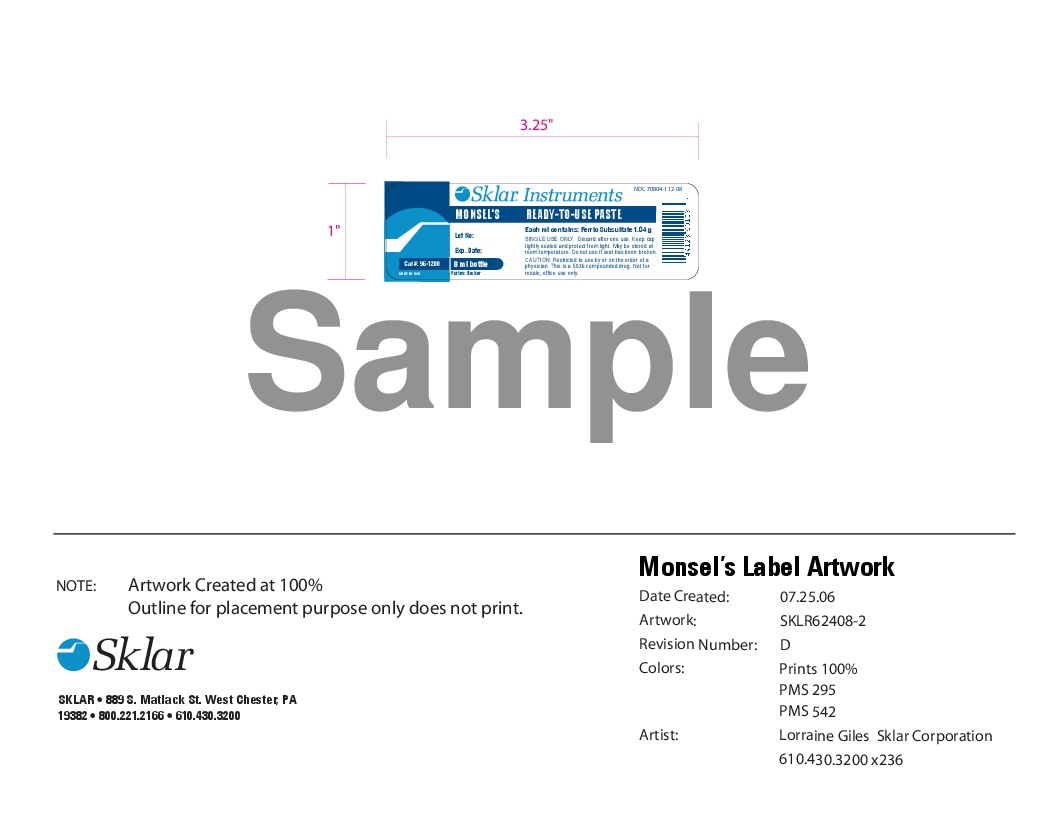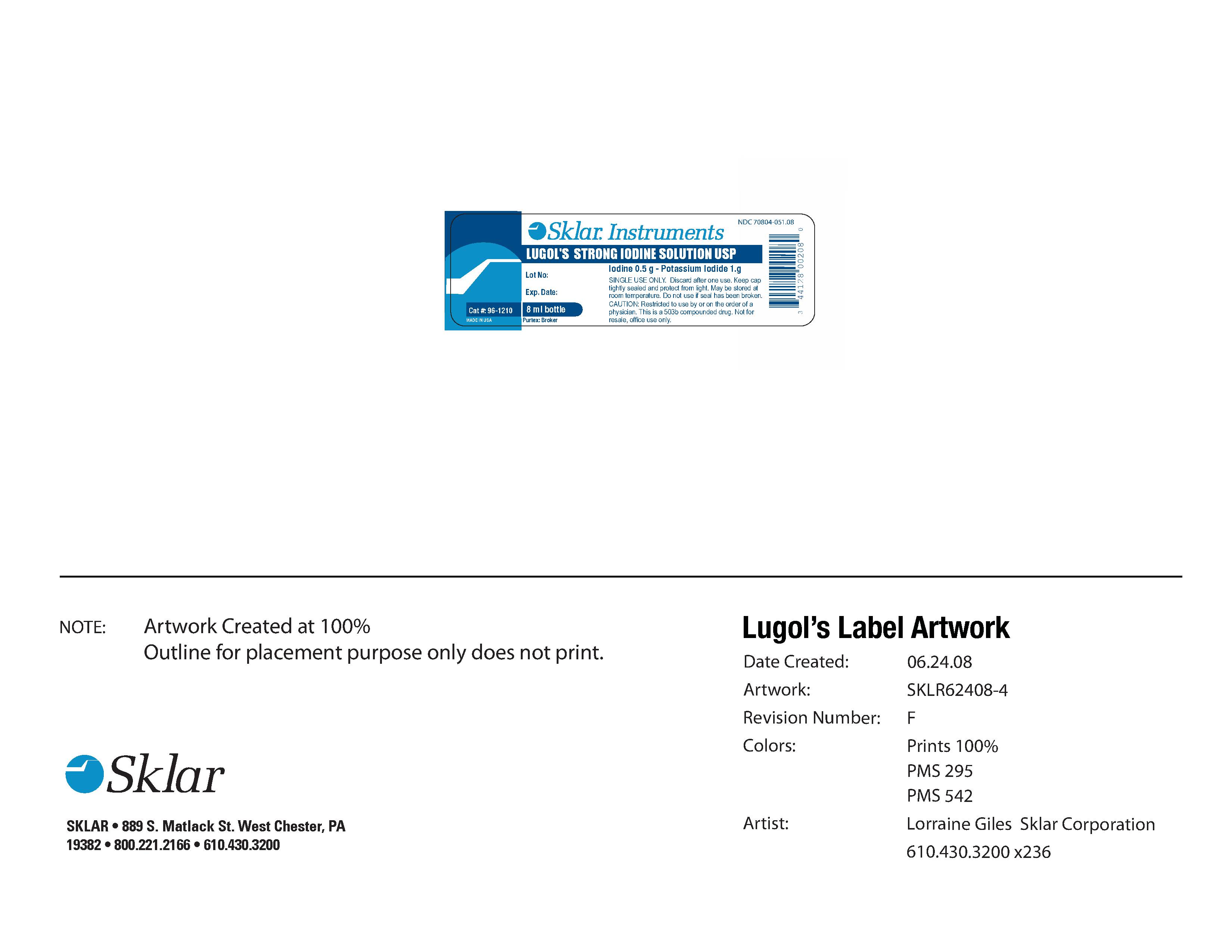 DRUG LABEL: Lugols Solution
NDC: 70804-005 | Form: SOLUTION
Manufacturer: PURTEX INC
Category: prescription | Type: HUMAN PRESCRIPTION DRUG LABEL
Date: 20191106

ACTIVE INGREDIENTS: IODINE 1 g/5 g

Restricted to use by or on the order of a licensed Physician. Keep cap tightly sealed and protect from light